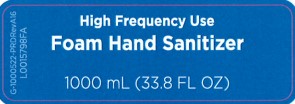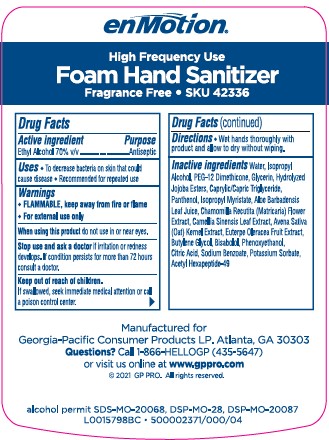 DRUG LABEL: enMotion Foam


NDC: 54622-486 | Form: SOLUTION
Manufacturer: Georgia-Pacific Consumer Products LP 
Category: otc | Type: HUMAN OTC DRUG LABEL
Date: 20260204

ACTIVE INGREDIENTS: ALCOHOL 70 mL/100 mL
INACTIVE INGREDIENTS: LEVOMENOL; PHENOXYETHANOL; CITRIC ACID MONOHYDRATE; SODIUM BENZOATE; POTASSIUM SORBATE; ACETYL HEXAPEPTIDE-49; WATER; ISOPROPYL ALCOHOL; PEG-12 DIMETHICONE; GLYCERIN; HYDROLYZED JOJOBA ESTERS (ACID FORM); GLYCERYL CAPRYLATE/CAPRATE; PANTHENOL; ISOPROPYL MYRISTATE; ALOE VERA LEAF; CHAMOMILE; GREEN TEA LEAF; OAT; ACAI; BUTYLENE GLYCOL

enMotion 486.002/486AD
Perch High Frequency Hand Sanitizer

Claims

enMotion

High Frequency Use

Foam Hand Sanitizer

Fragrance Free • SKU 42336

Active ingredient

Ethyl Alcohol 70% v/v

Purpose

Antiseptic

Uses

- To decrease bacteria on skin that could cause disease
- Recommended for repeated use

Warnings

FLAMMABLE, keep away from fire or flame

For external use only

When using this product

do not use in or near eyes.

Stop use and ask a doctor

if irritation or redness develops. If condition persists for more than 72 hours consult a doctor.

Keep out of reach of children.

If swallowed, seek immediate medical attention or call a poison control center.

Directions

- Wet hands thoroughly with product and allow to dry without wiping.

Inactive ingredients

Water, Isopropyl Alcohol, PEG-12 Dimethicone, Glycerin, Hydrolyzed Jojoba Esters,Caprylic/Capric Triglyceride, Panthenol, Isopropyl Myristate, Aloe Barbadensis Leaf Juice, Chamomilla Recutita (Matricaria) Flower Extract, Camellia Sinensis Leaf Extract, Avena Sativa (Oat) Kernel Extract, Euterpe Oleracea Fruit Extract, Butylene Glycol, Bisabolol, Phenoxyethanol, Citric Acid, Sodium Benzoate, Potassium Sorbate, Acetyl Hexapeptide-49

ADVERSE REACTION

Manufactured for Georgia-Pacific Consumer Products LP. Atlanta, GA 30303

Questions? Call 1-866-HELLOGP (435-5647)

or visit us online at www.gppro.com

(c) 2021 GP PRO. All rights reserved.

alcohol permit SDS-MO-20068, DSP-MO-28, DSP-MO-20087

principal display panel

High Frequency Use

Foam Hand Sanitizer

G-1000522-PRDRevA16

1000 mL (33.8 FL OZ)